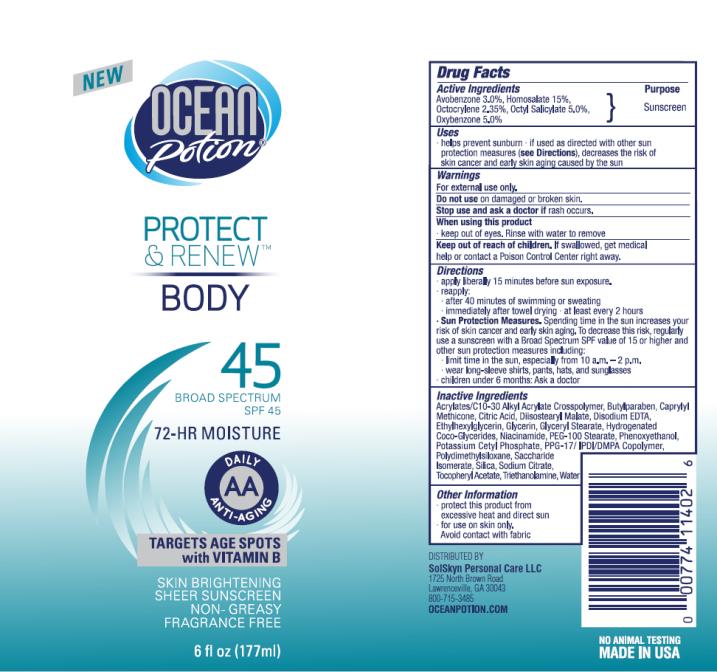 DRUG LABEL: OP Protect and Renew Body SPF 45
NDC: 70281-212 | Form: LOTION
Manufacturer: SolSkyn Personal Care LLC
Category: otc | Type: HUMAN OTC DRUG LABEL
Date: 20170201

ACTIVE INGREDIENTS: AVOBENZONE 3 g/100 g; HOMOSALATE 15 g/100 g; OCTOCRYLENE 2.35 g/100 g; OCTISALATE 5 g/100 g; OXYBENZONE 5 g/100 g
INACTIVE INGREDIENTS: CARBOMER INTERPOLYMER TYPE A (55000 CPS); BUTYLPARABEN; CAPRYLYL TRISILOXANE; CITRIC ACID MONOHYDRATE; DIISOSTEARYL MALATE; EDETATE DISODIUM ANHYDROUS; ETHYLHEXYLGLYCERIN; GLYCERIN; GLYCERYL MONOSTEARATE; HYDROGENATED COCO-GLYCERIDES; NIACINAMIDE; PEG-100 STEARATE; PHENOXYETHANOL; POTASSIUM CETYL PHOSPHATE; DIMETHICONE; SACCHARIDE ISOMERATE; SILICON DIOXIDE; SODIUM CITRATE; .ALPHA.-TOCOPHEROL ACETATE; TROLAMINE; WATER

OP-SPF45 6oz Protect Renew Body 72-hr Moisture

OP Protect & Renew Body SPF 45

Active Ingredients

Avobenzone 3.0%

Active Ingredients

Homosalate 15.0%

Active Ingredients

Octocrylene 2.35%

Active Ingredients

Octyl Salicylate 5.0%

Active Ingredients

Oxybenzone 5.0%

Purpose

Sunscreen

Uses

• Helps prevent sunburn.

• If used as directed with other sun protection measures (see Directions), decreases the risk of skin cancer and early skin aging caused by the sun.

Warnings:

• For external use only.

• Keep out of reach of children.

If swallowed, get medical help or contact a Poison Control Center right away.

Directions:

• Apply liberally 15 minutes before sun exposure.

• Re-apply:

• after 80 minutes of swimming or sweating

• immediately after towel drying

• at least every two hours

• Sun Protection Measures. Spending time in the sun increases your risk of skin cancer and early skin aging. To decrease this risk, regularly use a sunscreen with a Broad Spectrum SPF value of 15 or higher and other sun protection measures including:

• limit time in the sun, especially from 10 a.m.-2 p.m.

• wear long-sleeved shirts, pants, hats and sunglasses

• Children under 6 months: ask a doctor.

Inactive Ingredients

Acrylates/C10-30 Alkyl Acrylate Crossolymer, Butylparaben, Caprylyl Methicone, Citric Acid, Diisostearyl Malate, Disodium EDTA, Ethylhexylglycerin, Glycerin, Glyceryl Stearate, Hyrdogenated Coco-Glycerides, Niacinamide, PEG-100 Stearate, Phenoxyethanol, Potassium Cetyl Phosphate, PPG-17/IPDI/DMPA Coploymer, Polydimethylsiloxane, Saccaride Isomerate, Silica, Sodium Citrate, Tocopheryl Acetate, Triethanolamine, Water

Other Information

• Protect this product from excessive heat and direct sun.

• For use on skin only. Avoid contact with fabric.

PRINCIPAL DISPLAY PANEL

Ocean Potion
Protect
& Renew
Body
SPF 45
6 fl oz (177 mL)